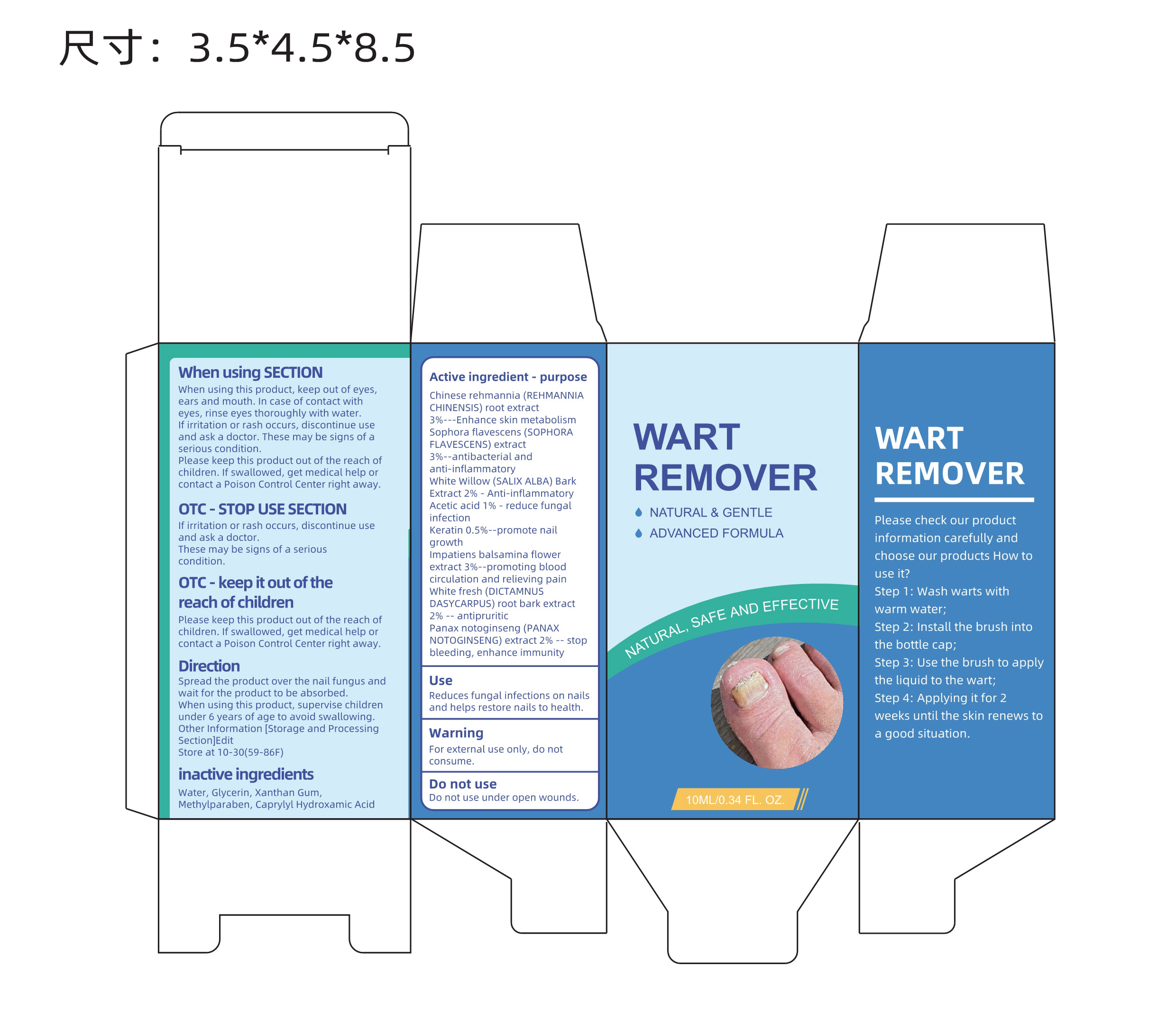 DRUG LABEL: WART REMOVER
NDC: 83619-001 | Form: LIQUID
Manufacturer: Shenzhen Derbit Technology Co., Ltd.
Category: otc | Type: HUMAN OTC DRUG LABEL
Date: 20240110

ACTIVE INGREDIENTS: SALIX ALBA BARK 2 g/100 mL; IMPATIENS BALSAMINA FLOWER 3 g/100 mL; REHMANNIA GLUTINOSA ROOT 3 g/100 mL; ACETIC ACID 1 g/100 mL; AMINO ACIDS, HAIR KERATIN 0.5 g/100 mL; DICTAMNUS DASYCARPUS ROOT BARK 2 g/100 mL; PANAX NOTOGINSENG ROOT 2 g/100 mL; SOPHORA FLAVESCENS ROOT 3 g/100 mL
INACTIVE INGREDIENTS: CAPRYLHYDROXAMIC ACID; WATER; GLYCERIN; XANTHAN GUM; METHYLPARABEN

Active ingredient

Chinese rehmannia (REHMANNIACHINENSIS) root extract 3%

Sophora flavescens (SOPHORAFLAVESCENS) extrac 3%

White Willow (SALIX ALBA) BarkExtract 2%

Acetic acid 1%

Keratin 0.5%

Impatiens balsamina flowerextract 3%

White fresh (DICTAMNUSDASYCARPUS) root bark extract 2%

Panax notoginseng (PANAXNOTOGINSENG) extract 2%

purpose

enhance skin metabolism

antibacterial andanti-inflammatory

Anti-inflammatory

reduce fungalinfection

promote nailgrowth

promoting bloodcirculation and relieving pain

antipruritic

stopbleeding, enhance immunity

use

Reduces fungal infections on nailsand helps restore nails to health.

Warning

For external use only, do not consume

Do not use under open wounds

When using SECTION

When using this product, keep out of eyes, ears and mouth. In case of contact with eyes, rinse eyes thoroughly with water. If irritation or rash occurs, discontinue use and ask a doctor. These may be signs of a serious condition Please keep this product out of the reach of children. If swallowed, get medical help or contact a Poison Control Center right away.

OTC-STOP USE SECTION

If irritation or rash occurs, discontinue useand ask a doctor.

These may be signs of a serious condition.

KEEP OUT OF REACH OF CHILDREN

Please keep this product out of the reach ofchildren. If swallowed, get medical help orcontact a Poison Control Center right away.

Direction

Spread the product over the nail fungus andwait for the product to be absorbed .When using this product , supervise childrenunder 6 years of age to avoid swallowing .Other Information (Storage and ProcessingSection) Edit Store at 10-30 (59-86F)

Other Information (Storage and Processing Section) Edit Store at 10-30 (59-86F)

inactive ingredients

Water , Glycerin , Xanthan Gum, Methylparaben , Caprylyl Hydroxamic Acid